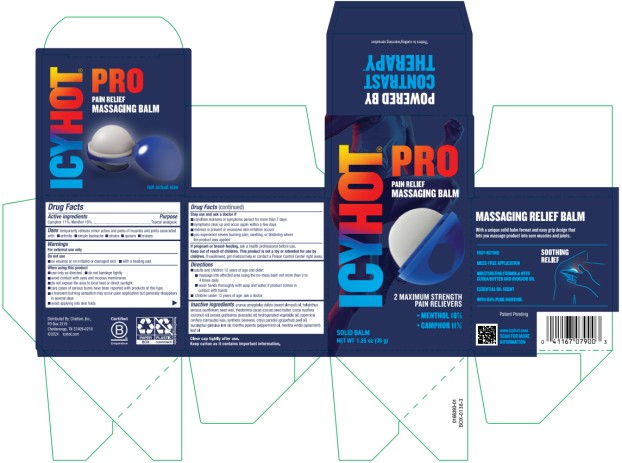 DRUG LABEL: Icy Hot Pro Pain Massaging Balm
NDC: 41167-0790 | Form: CREAM
Manufacturer: Chattem, Inc.
Category: otc | Type: HUMAN OTC DRUG LABEL
Date: 20260114

ACTIVE INGREDIENTS: MENTHOL .16 g/1 g; CAMPHOR (SYNTHETIC) .11 g/1 g
INACTIVE INGREDIENTS: ALMOND OIL; HELIANTHUS ANNUUS SEED WAX; COCOA BUTTER; COCONUT OIL; AVOCADO OIL; HYDROGENATED AVOCADO OIL; CARNAUBA WAX; SYNTHETIC BEESWAX; GRAPEFRUIT OIL; EUCALYPTUS OIL; PEPPERMINT OIL; SPEARMINT OIL

Icy Hot Pro Pain Relief Massaging Balm

Icy Hot PRO Pain Relief Massaging Balm

Drug Facts

Active ingredient

Camphor 11%

Menthol 16%

Purpose

Topical analgesic

Uses

temporarily relieves minor aches and pains of muscles and joints associated with:

- arthritis
- simple backache
- strains
- sprains
- bruises

Warnings

For external use only

Do not use

- on wounds or on irritated or damaged skin
- with a heating pad

When using this product

- use only as directed
- do not bandage tightly
- avoid contact with eyes and mucous membranes
- do not expose the area to local heat or direct sunlight
- rare cases of serious burns have been reported with products of this type
- a transient burning sensation may occur upon application but generally disappears in several days
- avoid applying into skin folds

Stop use and ask a doctor if

- condition worsens or symptoms persist for more than 7 days
- symptoms clear up and occur again within a few days
- redness is present or excessive skin irritation occurs
- you experience severe burning pain, swelling, or blistering where the product was applied

If pregnant or breast-feeding,

ask a health professional before use.

Keep out of reach of children.

This product is not a toy or intended for use by children.

If swallowed, get medical help or contact a Poison Control Center right away.

Directions

- adults and children 12 years of age and older:
  - massage into affected area using the no-mess balm not more than 3 to 4 times daily
  - wash hands thoroughly with soap and water if product comes in contact with hands
- children under 12 years of age: ask a doctor

Inactive ingredients

prunus amygdalus dulcis (sweet almond) oil, helianthus annuus (sunflower) seed wax, theobroma cacao (cocoa) seed butter, cocos nucifera (coconut) oil, persea gratissima (avocado) oil, hydrogenated vegetable oil, copernicia cerifera (carnauba) wax, synthetic beeswax, citrus paradisi (grapefruit) peel oil, eucalyptus globulus leaf oil, mentha piperita (peppermint) oil, mentha viridis (spearmint) leaf oil

Close cap tightly after use. Keep carton as it contains important information.

Keep carton as it contains important information.

PRINCIPAL DISPLAY PANEL

ICY HOT Pro Pain Relief
Massaging Balm
NET WT 1.25 OZ (35 g)